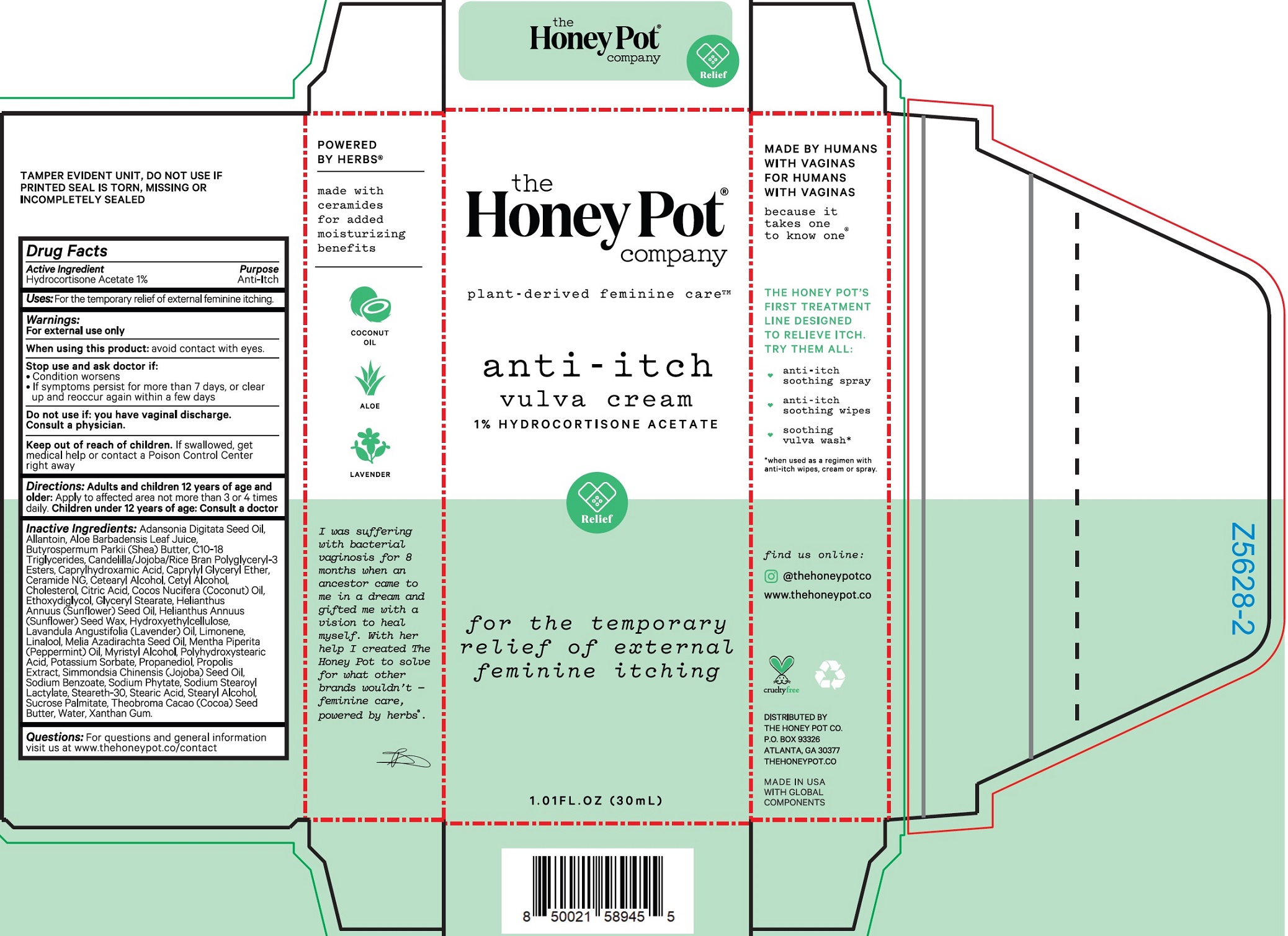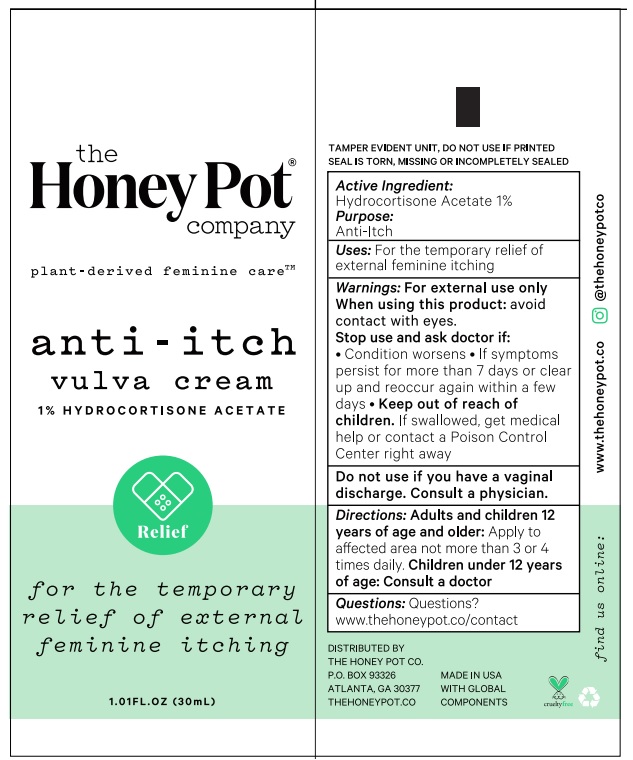 DRUG LABEL: Anti-Itch Vulva Cream 1 Hydrocortisone Acetate
NDC: 82637-9455 | Form: CREAM
Manufacturer: The Honey Pot Company LLC
Category: otc | Type: HUMAN OTC DRUG LABEL
Date: 20240801

ACTIVE INGREDIENTS: HYDROCORTISONE ACETATE 10 mg/1 mL
INACTIVE INGREDIENTS: HYDROXYETHYL CELLULOSE, UNSPECIFIED; LAVENDER OIL; LIMONENE, (+)-; LINALOOL, (+/-)-; AZADIRACHTA INDICA SEED OIL; PEPPERMINT OIL; MYRISTYL ALCOHOL; POTASSIUM SORBATE; PROPANEDIOL; PROPOLIS WAX; JOJOBA OIL; SODIUM BENZOATE; PHYTATE SODIUM; SODIUM STEAROYL LACTYLATE; STEARETH-30; STEARIC ACID; STEARYL ALCOHOL; SUCROSE PALMITATE; COCOA BUTTER; WATER; XANTHAN GUM; ADANSONIA DIGITATA SEED OIL; ALLANTOIN; ALOE VERA LEAF; SHEA BUTTER; C10-18 TRIGLYCERIDES; CANDELILLA WAX; CAPRYLHYDROXAMIC ACID; CAPRYLYL GLYCERYL ETHER; CERAMIDE NG; CETOSTEARYL ALCOHOL; CETYL ALCOHOL; CHOLESTEROL; CITRIC ACID MONOHYDRATE; COCONUT OIL; DIETHYLENE GLYCOL MONOETHYL ETHER; GLYCERYL MONOSTEARATE; SUNFLOWER OIL; HELIANTHUS ANNUUS SEED WAX

Anti-Itch Vulva Cream 1 % Hydrocortisone Acetate

Active Ingredient

Hydrocortisone Acetate 1%

Purpose

Anti-Itch

Uses:

For the temporary relief of external feminine itching.

Warnings:

For external use only

When using this product:

avoid contact with eyes.

Stop use and ask doctor if:

- Condition worsens
- If symptoms persist for more than 7 days, or clear up and reoccur again within a few days

Do not use if:

you have vaginal discharge. Consult a physician.

Keep out of reach of children.

If swallowed, get medical help or contact a Poison Control Center right away

Directions:

Apply to affected area not more than 3 to 4 times daily. Adults and children 12 years of age and older: Children under 12 years of age: Consult a doctor

Inactive Ingredients:

Adansonia Digitata Seed Oil, Allantoin, Aloe Barbadensis Leaf Juice, Butyrospermum Parkii (Shea) Butter, C10-18 Triglycerides, Candelilla/Jojoba/Rice Bran Polyglyceryl-3 Esters, Caprylhydroxamic Acid, Caprylyl Glyceryl Ether, Ceramide NG, Cetearyl Alcohol, Cetyl Alcohol, Cholesterol, Citric Acid, Cocos Nucifera (Coconut) Oil, Ethoxydiglycol, Glyceryl Stearate, Helianthus Annuus (Sunflower) Seed Oil, Helianthus Annuus (Sunflower) Seed Wax, Hydroxyethylcellulose, Lavandula Angustifolia (Lavender) Oil, Limonene, Linalool, Melia Azadirachta Seed Oil, Mentha Piperita (Peppermint) Oil, Myristyl Alcohol, Polyhydroxystearic Acid, Potassium Sorbate, Propanediol, Propolis Extract, Simmondsia Chinensis (Jojoba) Seed Oil, Sodium Benzoate, Sodium Phytate, Sodium Stearoyl Lactylate, Steareth-30, Stearic Acid, Steary Alcohol, Sucrose Palmitate, Theobroma Cacao (Cocoa) Seed Butter, Water, Xanthan Gum

Questions:

For questions and general information visit us at www.thehoneypot.co/contact